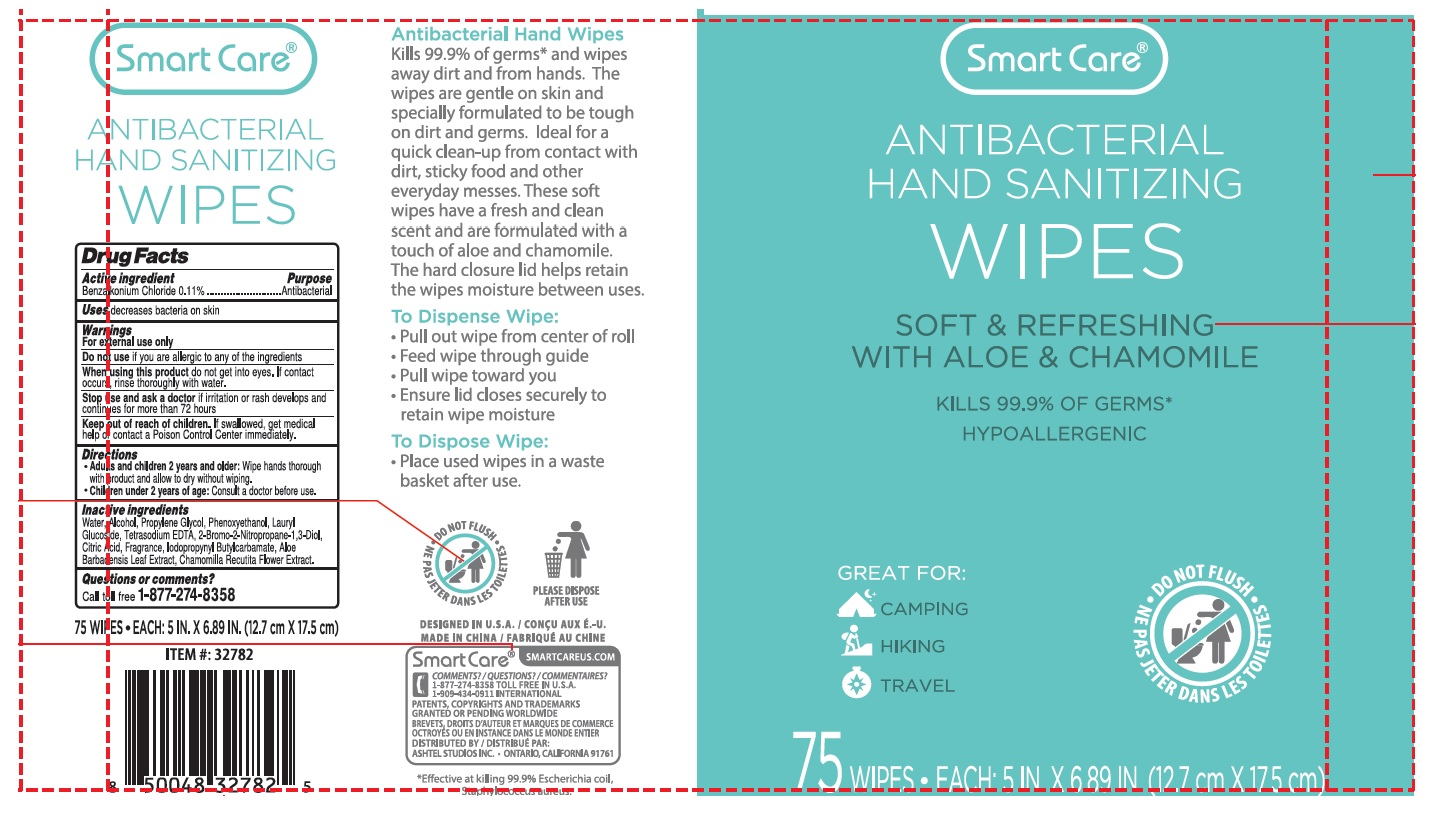 DRUG LABEL: Smart Care Antibacterial Hand Sanitizing Wipes
NDC: 70108-077 | Form: CLOTH
Manufacturer: Ashtel Studios, Inc.
Category: otc | Type: HUMAN OTC DRUG LABEL
Date: 20250725

ACTIVE INGREDIENTS: BENZALKONIUM CHLORIDE 0.11 g/100 mL
INACTIVE INGREDIENTS: WATER; ALCOHOL; PROPYLENE GLYCOL; PHENOXYETHANOL; LAURYL GLUCOSIDE; EDETATE SODIUM; BRONOPOL; CITRIC ACID MONOHYDRATE; IODOPROPYNYL BUTYLCARBAMATE; ALOE VERA LEAF; CHAMOMILE

Smart Care® ANTIBACTERIAL HAND SANITIZING WIPES

Active ingredient

Benzalkonium Chloride 0.11%

Purpose

Antibacterial

Uses

decreases bacteria on skin

Warnings

For external use only

Do not use if you are allergic to any of the ingredients

When using this product do not get into eyes. If contact occurs, rinse thoroughly with water.

Stop use and ask a doctor if irritation or rash develops and continues for more than 72 hours

Keep out of reach of children. If swallowed, get medical help or contact a Poison Control Center immediately.

Directions

- Adults and children 2 years and older: Wipe hands thorough with product and allow to dry without wiping.
- Children under 2 years of age: Consult a doctor before use.

Inactive ingredients

Water, Alcohol, Propylene Glycol, Phenoxyethanol, Lauryl Glucoside, Tetrasodium EDTA, 2-Bromo-2-Nitropropane-1,3-Diol, Citric Acid, Fragrance, Iodopropynyl Butylcarbamate, Aloe Barbadensis Leaf Extract, Chamomilla Recutita Flower Extract.

Questions or comments?

Call toll free 1-877-274-8358

SOFT & REFRESHING WITH ALOE & CHAMOMILE

KILLS 99.9% OF GERMS*

HYPOALLERGENIC

GREAT FOR:
CAMPING
HIKING
TRAVEL

DO NOT FLUSH

EACH 5 IN. X 6.89 IN. (12.7 cm X 17.5 cm)

Antibacterial Hand Wipes

Kills 99.9% of germs* and wipes away dirt and from hands. The wipes are gentle on skin and specially formulated to be tough on dirt and germs. Ideal for a quick clean-up from contact with dirt, sticky food and other everyday messes. These soft wipes have a fresh and clean scent and are formulated with a touch of aloe and chamomile. The hard closure lid helps retain the wipes moisture between uses.

To Dispense Wipe:• Pull out wipe from center of roll
• Feed wipe through guide
• Pull wipe toward you
• Ensure lid closes securely to retain wipe moisture

To Dispose Wipe:• Place used wipes in a waste basket after use.

PLEASE DISPOSE AFTER USE

DESIGNED IN U.S.A.

MADE IN CHINA

COMMENTS? / QUESTIONS?
1-877-274-8358 TOLL FREE IN U.S.A.
1-909-434-0911 INTERNATIONAL PATENTS, COPYRIGHTS AND TRADEMARKS GRANTED OR PENDING WORLDWIDE

DISTRIBUTED BY:
ASHTEL STUDIOS INC. • ONTARIO, CALIFORNIA 91761

SMARTCAREUS.COM

*Effective at killing 99.9% Escherichia coil, Staphylococcus aureus.